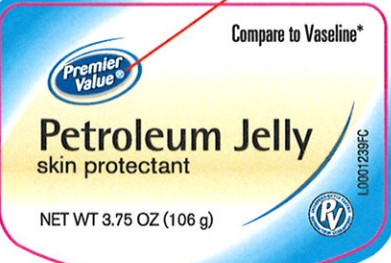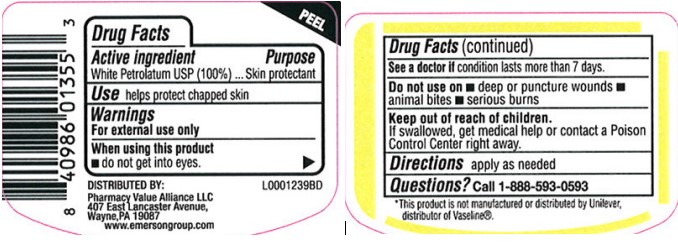 DRUG LABEL: Petroleum Skin Protectant
NDC: 68016-069 | Form: JELLY
Manufacturer: Pharmacy Value Alliance, LLC
Category: otc | Type: HUMAN OTC DRUG LABEL
Date: 20260205

ACTIVE INGREDIENTS: PETROLATUM 1 g/1 g

Premier Value 069.001/069AA
Petroleum Jelly

Active ingredient

White petrolatum USP (100%)

Purpose

Skin protectant

Uses

helps protect chapped skin

Warnings

For external use only

When using this product

- do not get into eyes

See a doctor if

condition lasts more than 7 days.

Do not use on

- deep or puncture wounds
- animal bites
- serious burns

Keep out of reach of children.

If swallowed, get medical help or contact a Poison Control Center right away.

Directions

apply as needed

Inactive ingredients

None

Questions?

Call 1-888-593-0593

Dislcaimer

*This product is not manufactured or distributed by Unliever, distributor of Vaseline®.

Adverse Reactions

DISTRIBUTED BY:

Pharmacy Value Alliance LLC

407 East Lancaster Avenue,

Wayne, PA 19087

www.emersongroup.com

principal display panel

Compare to Vaseline*

Premier

Value®

Petroleum Jelly

skin protectant

NET WT 3.75 OZ (106 g)